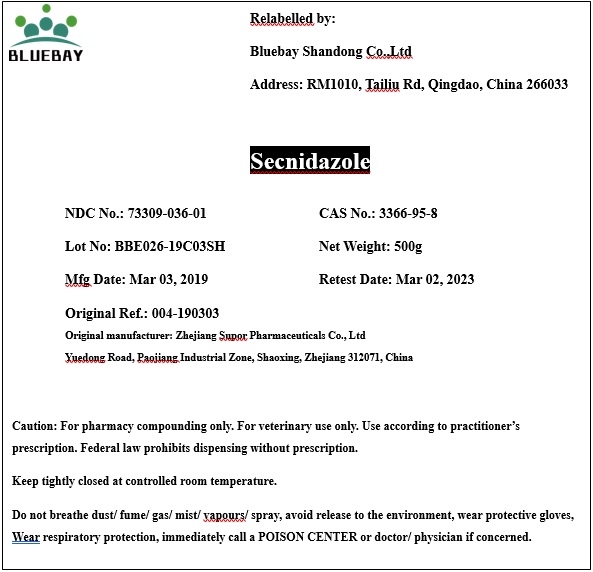 DRUG LABEL: Secnidazole
NDC: 73309-036 | Form: POWDER
Manufacturer: BLUEBAY SHANDONG CO.,LTD
Category: other | Type: BULK INGREDIENT
Date: 20190927

ACTIVE INGREDIENTS: SECNIDAZOLE 1 g/1 g

Secnidazole